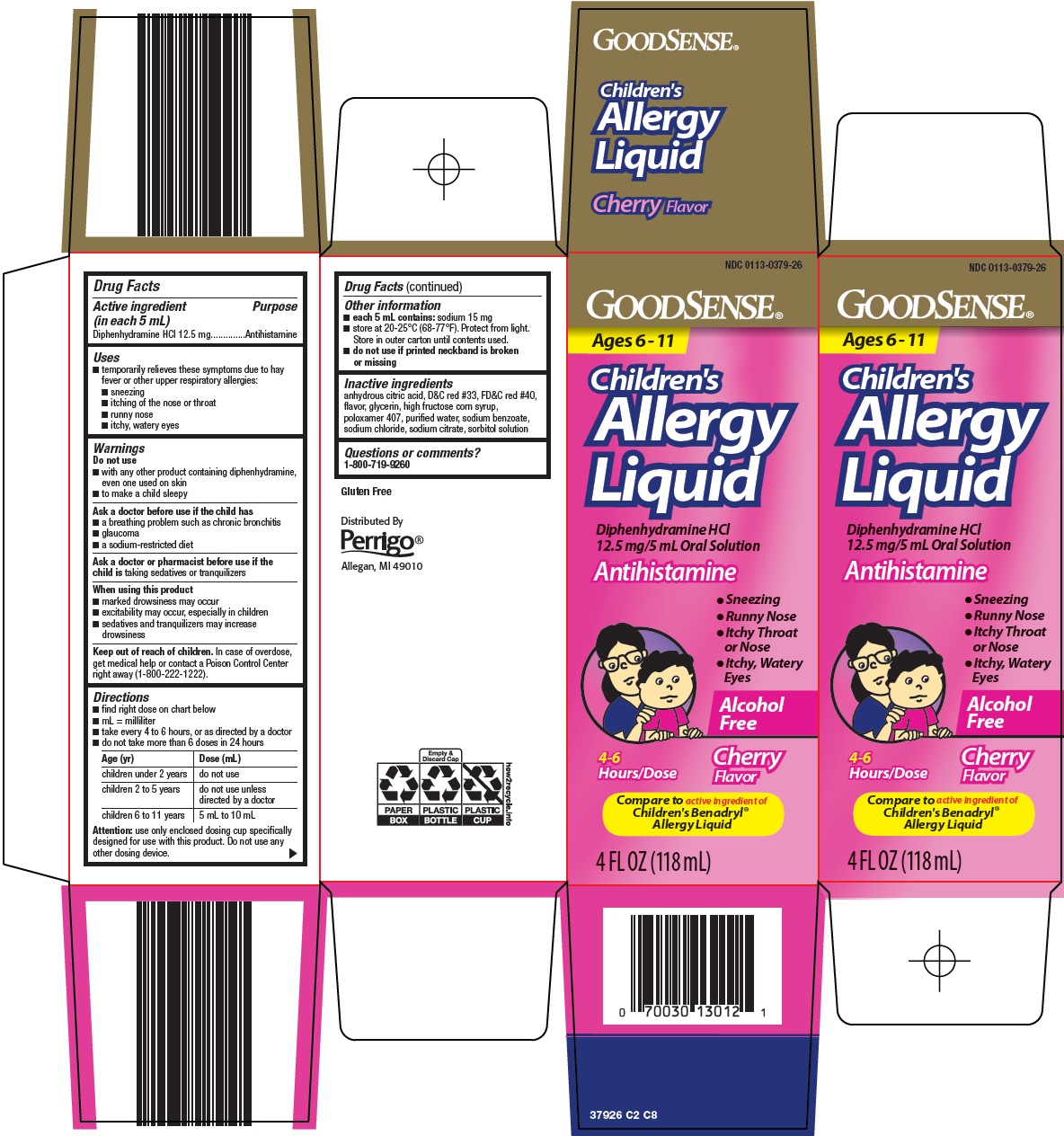 DRUG LABEL: good sense allergy
NDC: 0113-0379 | Form: SOLUTION
Manufacturer: L. Perrigo Company
Category: otc | Type: HUMAN OTC DRUG LABEL
Date: 20260211

ACTIVE INGREDIENTS: DIPHENHYDRAMINE HYDROCHLORIDE 12.5 mg/5 mL
INACTIVE INGREDIENTS: ANHYDROUS CITRIC ACID; D&C RED NO. 33; FD&C RED NO. 40; HIGH FRUCTOSE CORN SYRUP; POLOXAMER 407; WATER; SODIUM BENZOATE; SODIUM CHLORIDE; SODIUM CITRATE, UNSPECIFIED FORM; SORBITOL SOLUTION; GLYCERIN

Perrigo Children’s Allergy Liquid Drug Facts

Active ingredient (in each 5 mL)

Diphenhydramine HCl 12.5 mg

Purpose

Antihistamine

Uses

- temporarily relieves these symptoms due to hay fever or other upper respiratory allergies:
- sneezing
- itching of the nose or throat
- runny nose
- itchy, watery eyes

Warnings

Do not use

- with any other product containing diphenhydramine, even one used on skin
- to make a child sleepy

Ask a doctor before use if the child has

- a breathing problem such as chronic bronchitis
- glaucoma
- a sodium-restricted diet

Ask a doctor or pharmacist before use if the child is

taking sedatives or tranquilizers

When using this product

- marked drowsiness may occur
- excitability may occur, especially in children
- sedatives and tranquilizers may increase drowsiness

Keep out of reach of children.

In case of overdose, get medical help or contact a Poison Control Center right away (1-800-222-1222).

Directions

- find right dose on chart below
- mL = milliliter
- take every 4 to 6 hours, or as directed by a doctor
- do not take more than 6 doses in 24 hours

Age (yr) | Dose (mL)
children under 2 years | do not use
children 2 to 5 years | do not use unless directed by a doctor
children 6 to 11 years | 5 mL to 10 mL

Attention: use only enclosed dosing cup specifically designed for use with this product. Do not use any other dosing device.

Other information

- each 5 mL contains: sodium 15 mg
- store at 20-25°C (68-77°F). Protect from light. Store in outer carton until contents used.
- do not use if printed neckband is broken or missing

Inactive ingredients

anhydrous citric acid, D&C red #33, FD&C red #40, flavor, glycerin, high fructose corn syrup, poloxamer 407, purified water, sodium benzoate, sodium chloride, sodium citrate, sorbitol solution

Questions or comments?

1-800-719-9260

Principal Display Panel

GOODSENSE®

Ages 6 – 11

Children’s

Allergy Liquid

Diphenhydramine HCl

12.5 mg/5 mL Oral Solution

Antihistamine

● Sneezing

● Runny Nose

● Itchy Throat or Nose

● Itchy, Watery Eyes

Alcohol Free

4-6 Hours/Dose

Cherry Flavor

Compare to active ingredient of Children’s Benadryl® Allergy Liquid

4 FL OZ (118 mL)